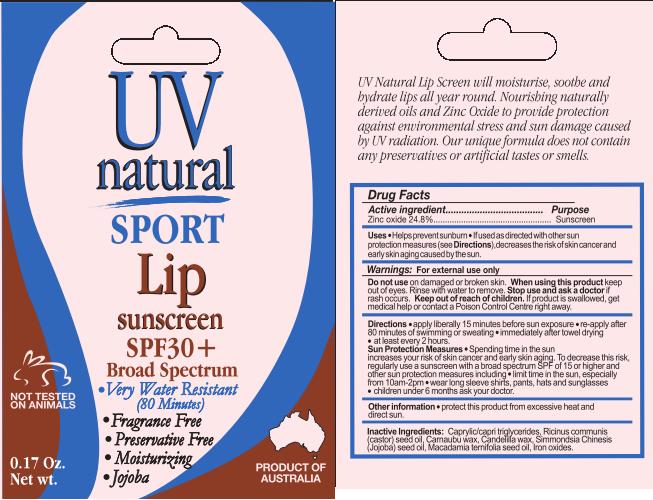 DRUG LABEL: Sunscreen Sport Lip
NDC: 29565-500 | Form: LOTION
Manufacturer: UV Natural International Pty Ltd
Category: otc | Type: HUMAN OTC DRUG LABEL
Date: 20120510

ACTIVE INGREDIENTS: ZINC OXIDE 1.24 mL/5 mL
INACTIVE INGREDIENTS: CASTOR OIL; TRICAPRIN; CARNAUBA WAX; CANDELILLA WAX; MACADAMIA OIL; JOJOBA OIL

ACTIVE INGREDIENT

Zinc oxide 24.8%

PURPOSE

Sunscreen

Uses

- Helps prevent sunburn
- If used as directed with other sun protection measures (see Directions), decreases the risk of skin cancer and early skin aging caused by the sun

WARNINGS

For external use only

Do not use on damaged or broken skin.

When using this product keep out of eyes. Rinse with water to remove.

Stop use and ask a doctor if rash occurs.

Keep out of reach of children. If product is swallowed, get medical help or contact a Poison Control Centre right away.

Directions

- apply liberally 15 minutes before sun exposure
- re-apply after 80 minutes of swimming or sweating
- immediately after towel drying
- at least every two hours

Sun Protection Measures: Spending time in the sun increases your risk of skin cancer and early skin aging. To decrease this risk, regularly use a sunscreen with a broad spectrum SPF of 15 or higher and other sun protection measures including:

- limit time in sun, especially from 10am-2pm
- wear long sleeve shirts, pants, hats and sunglasses

Children under 6 months ask your doctor.

STORAGE AND HANDLING

protect this product from excessive heat and direct sun

INACTIVE INGREDIENT

Caprilic/capric triglycerides, Ricinus communis (castor) seed oil, Carnaubu wax, Candelilla wax, Simmondsia Chinesis (Jojoba) seed oil, Macadamia ternifolia seed oil, Iron oxides

PACKAGE LABEL

- Very Water Resistant (80 Minutes)
- Fragrance Free
- Preservative Free
- Moisturizing
- Jojoba